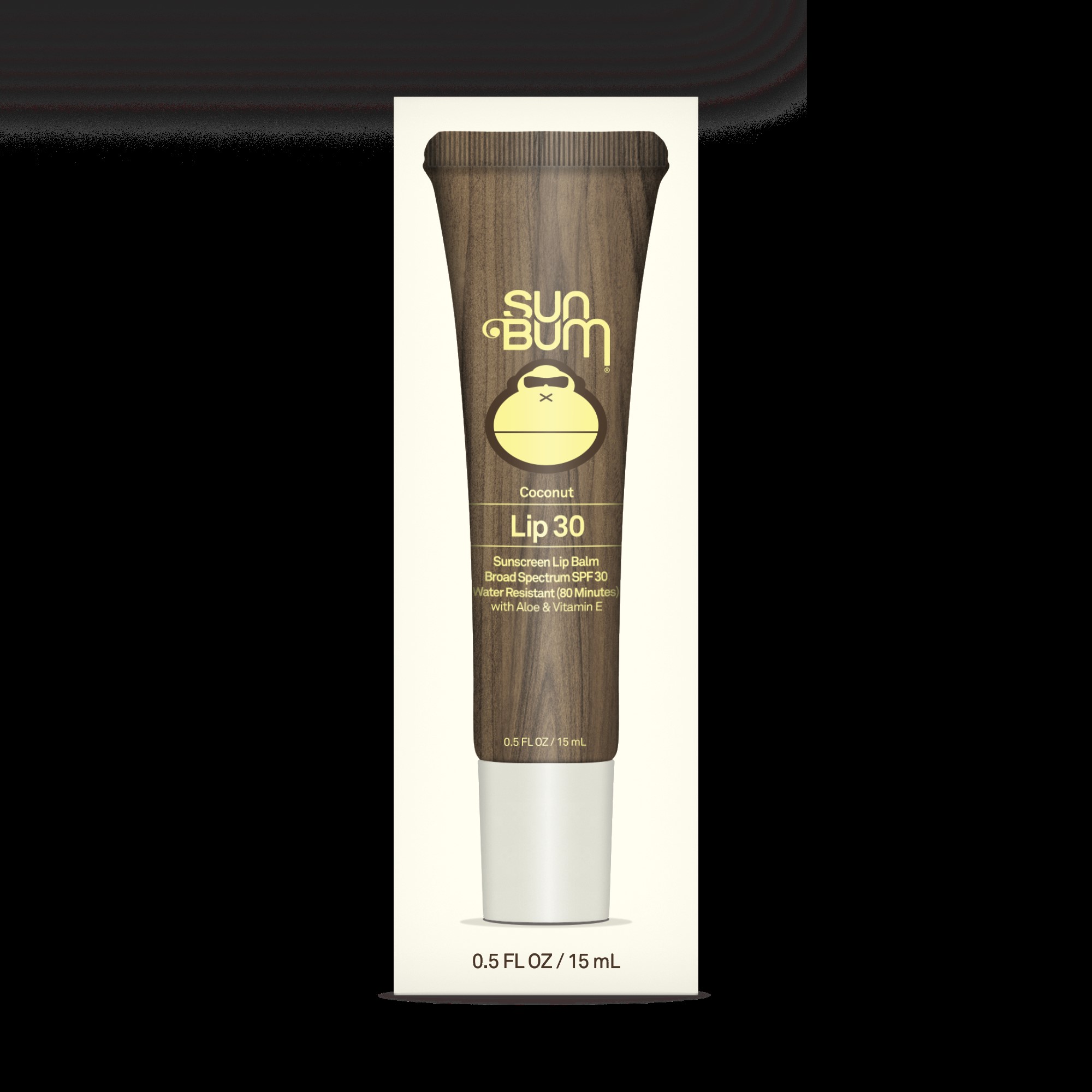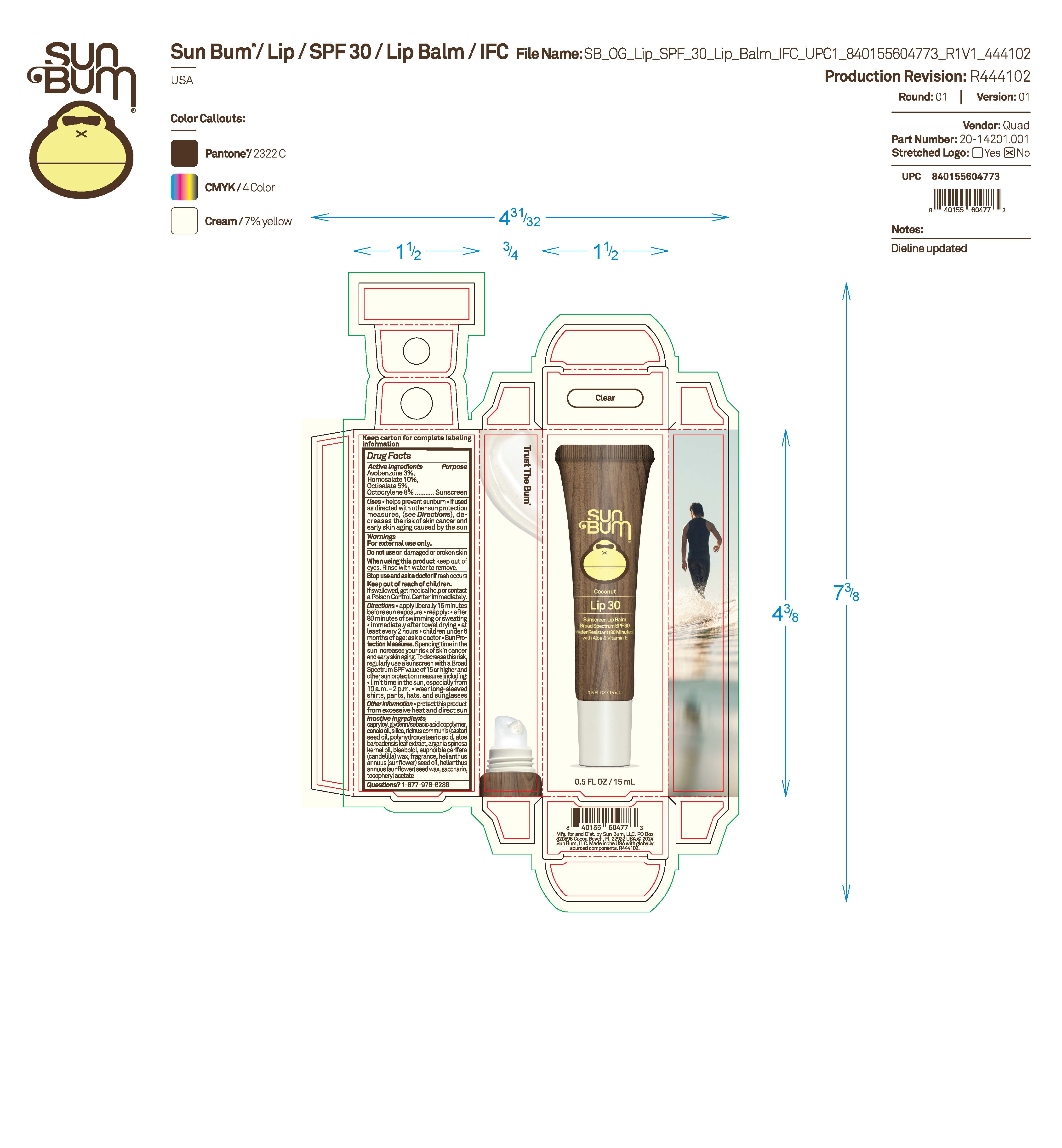 DRUG LABEL: Sun Bum Coconut Lip 30 Sunscreen Lip Balm
NDC: 69039-669 | Form: OINTMENT
Manufacturer: Sun Bum, LLC
Category: otc | Type: HUMAN OTC DRUG LABEL
Date: 20250821

ACTIVE INGREDIENTS: HOMOSALATE 100 mg/1 mL; OCTOCRYLENE 80 mg/1 mL; AVOBENZONE 30 mg/1 mL; OCTISALATE 50 mg/1 mL
INACTIVE INGREDIENTS: RICINUS COMMUNIS (CASTOR) SEED OIL; HELIANTHUS ANNUUS (SUNFLOWER) SEED OIL; SACCHARIN; POLYHYDROXYSTEARIC ACID (2300 MW); EUPHORBIA CERIFERA (CANDELILLA) WAX; .ALPHA.-TOCOPHEROL ACETATE; CAPRYLOYL GLYCERIN/SEBACIC ACID COPOLYMER (2000 MPA.S); HELIANTHUS ANNUUS (SUNFLOWER) SEED WAX; CANOLA OIL; SILICA; ALOE BARBADENSIS LEAF; ARGANIA SPINOSA KERNEL OIL; BISABOLOL

Sun Bum Coconut Lip 30 Sunscreen Lip Balm

Active ingredients

Avobenzone 3%, Homosalate 10%, Octisalate 5%, Octocrylene 8%

Purpose

Sunscreen

Uses

• helps prevent sunburn • if used as directed with other sun protection measures, (see Directions) decreases the risk of skin cancer and early skin aging caused by the sun

Warnings

For external use only

Do not use on damaged or broken skin

When using this product keep out of eyes. Rinse with water to remove.

Stop use and ask a doctor if rash occurs

Keep out of reach of children. If swallowed, get medical help or contact a Poison Control Center immediately.

Warnings

Keep Out Of Reach Of Children

Directions

• apply liberally 15 minutes before sun exposure

• reapply: • after 80 minutes of swimming or sweating • immediately after towel drying • at least every 2 hours

• children under 6 months of age: ask a doctor

• Sun Protection Measures. Spending time in the sun increases your risk of skin cancer and early skin aging. To decrease this risk, regularly use a sunscreen with a Broad Spectrum SPF value of 15 or higher and other sun protection measures including:

• limit time in the sun, especially from 10 a.m.- 2 p.m.

• wear long-sleeved shirts, pants, hats and sunglasses

Directions

• apply liberally 15 minutes before sun exposure

Other information

protect this product from excessive heat and direct sun

Inactive ingredients

capryloyl glycerin/sebacic acid copolymer, canola oil, silica, ricinus communis (castor) seed oil, polyhydroxystearic acid, aloe barbadensis leaf extract, argania spinosa kernel oil, bisabolol, euphorbia cerifera (candelilla) wax, fragrance, helianthus annuus (sunflower) seed oil, helianthus annuus (sunflower) seed wax, saccharin, tocopheryl acetate

Questions

Questions? 1-877-978-6286